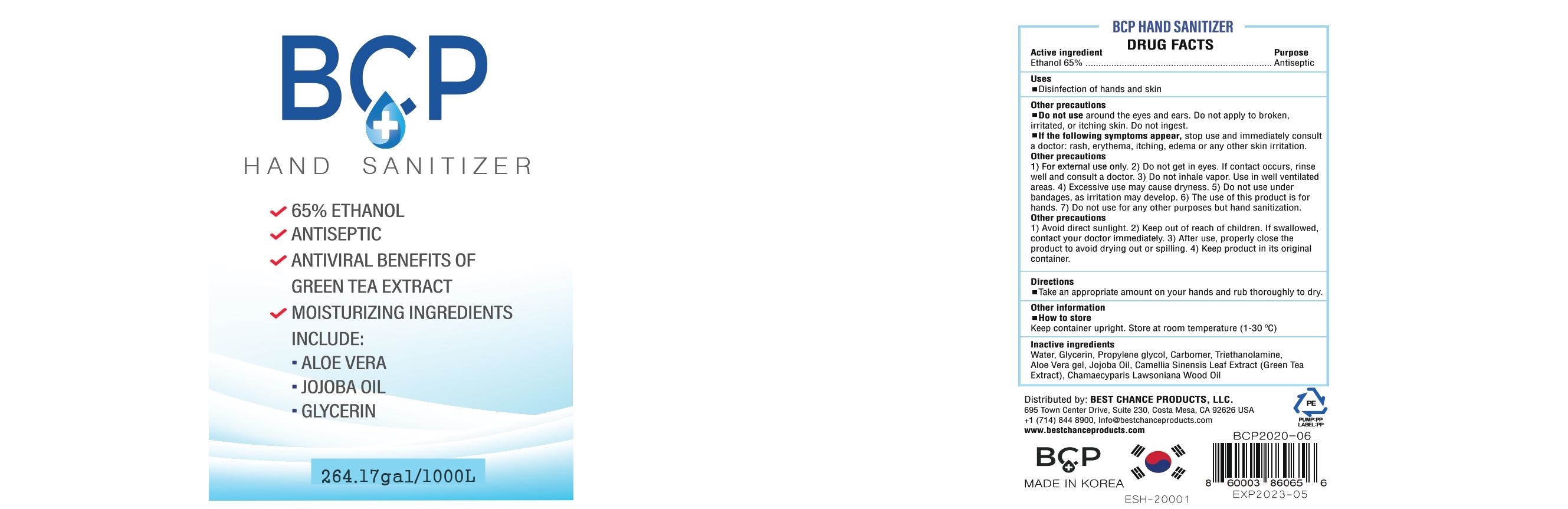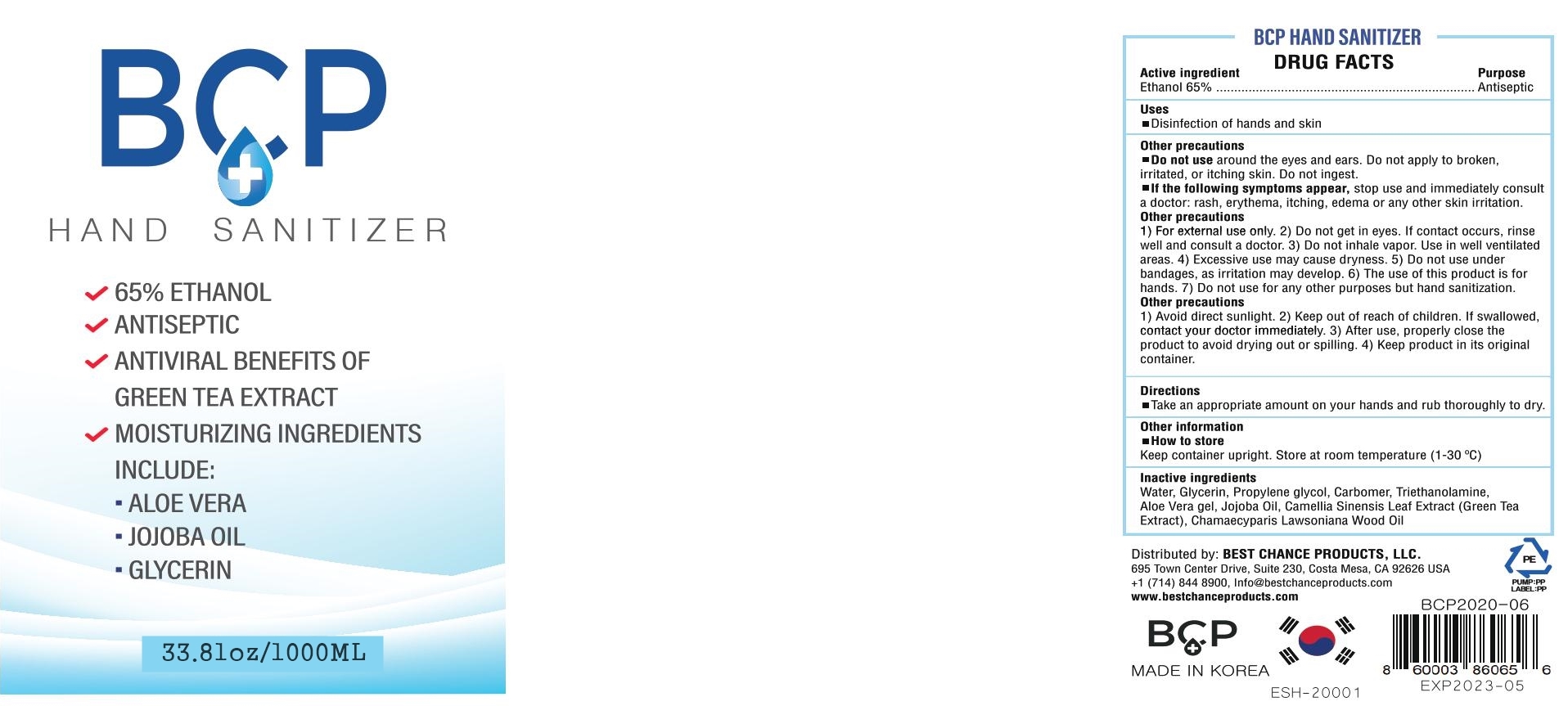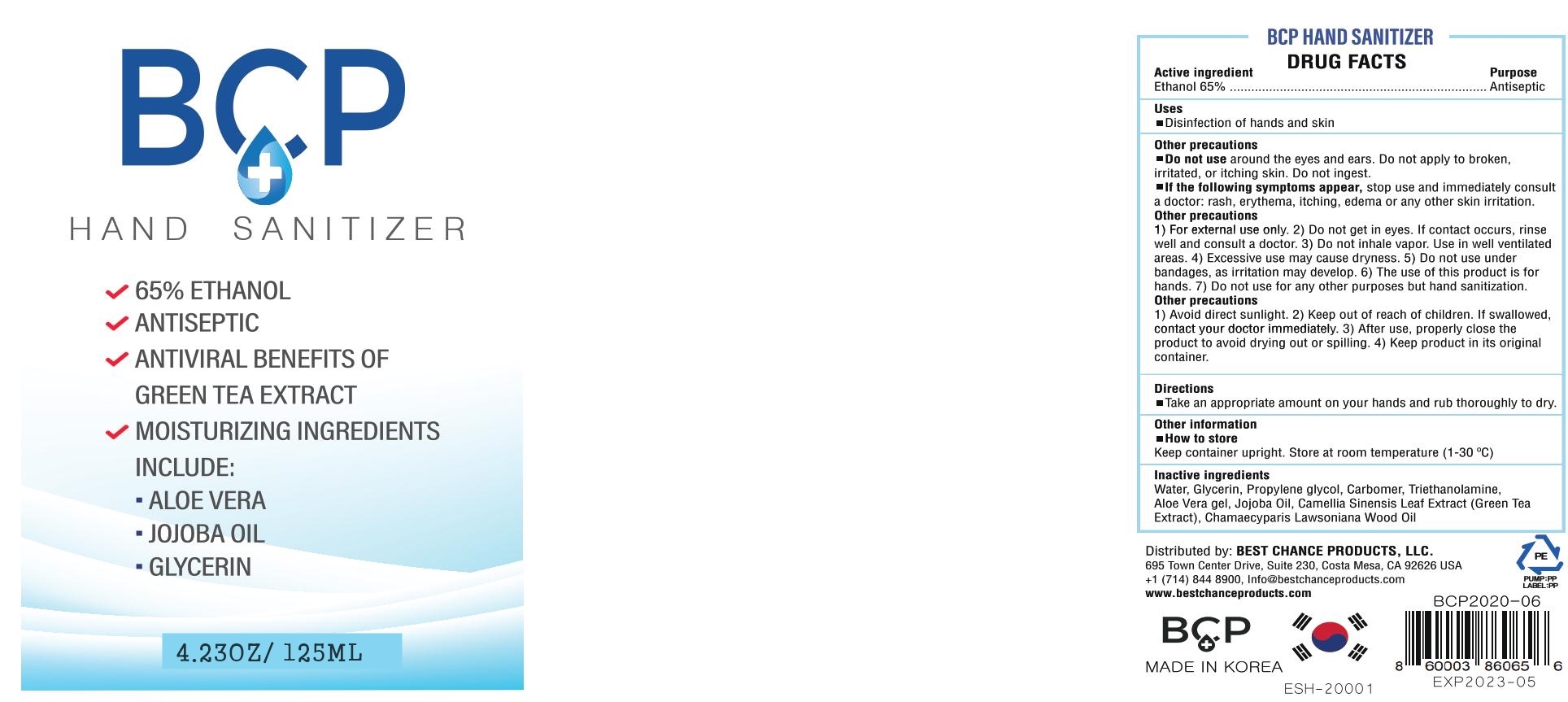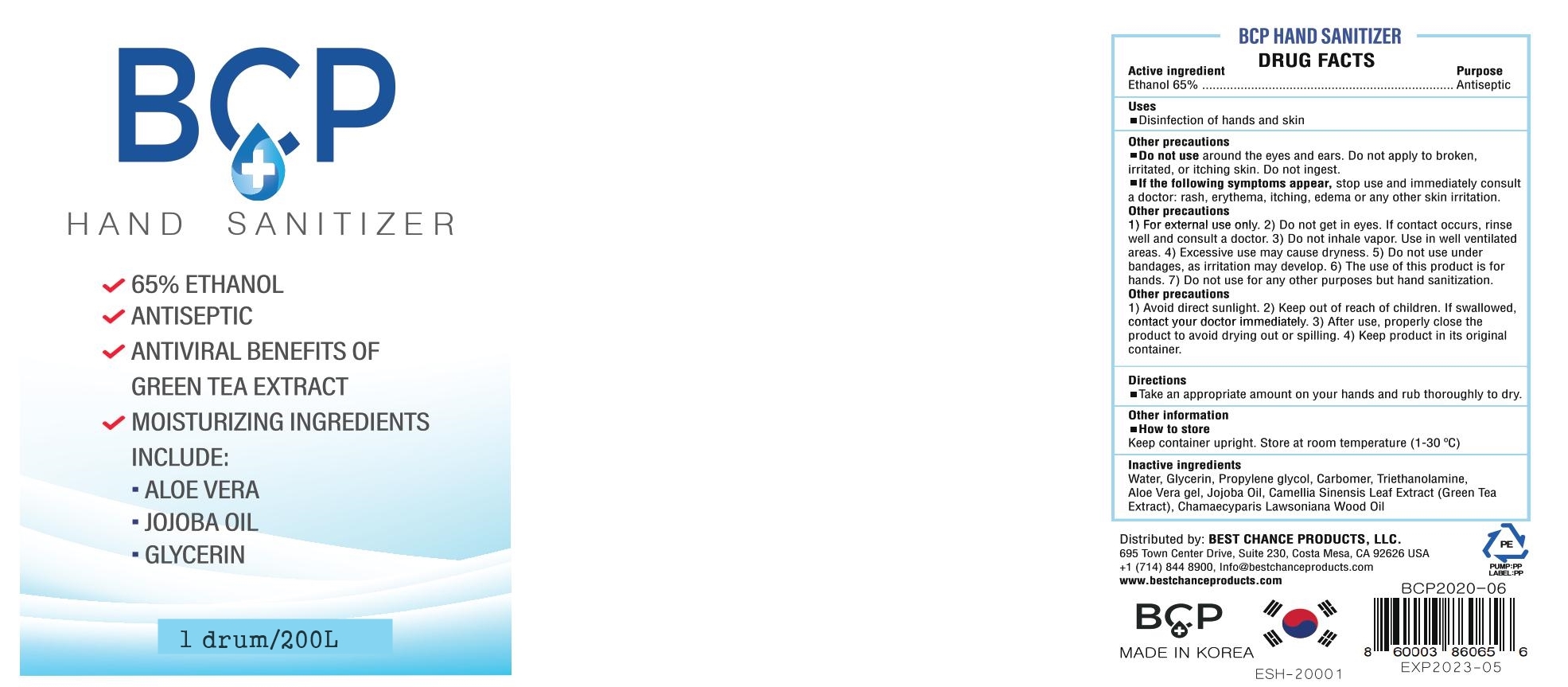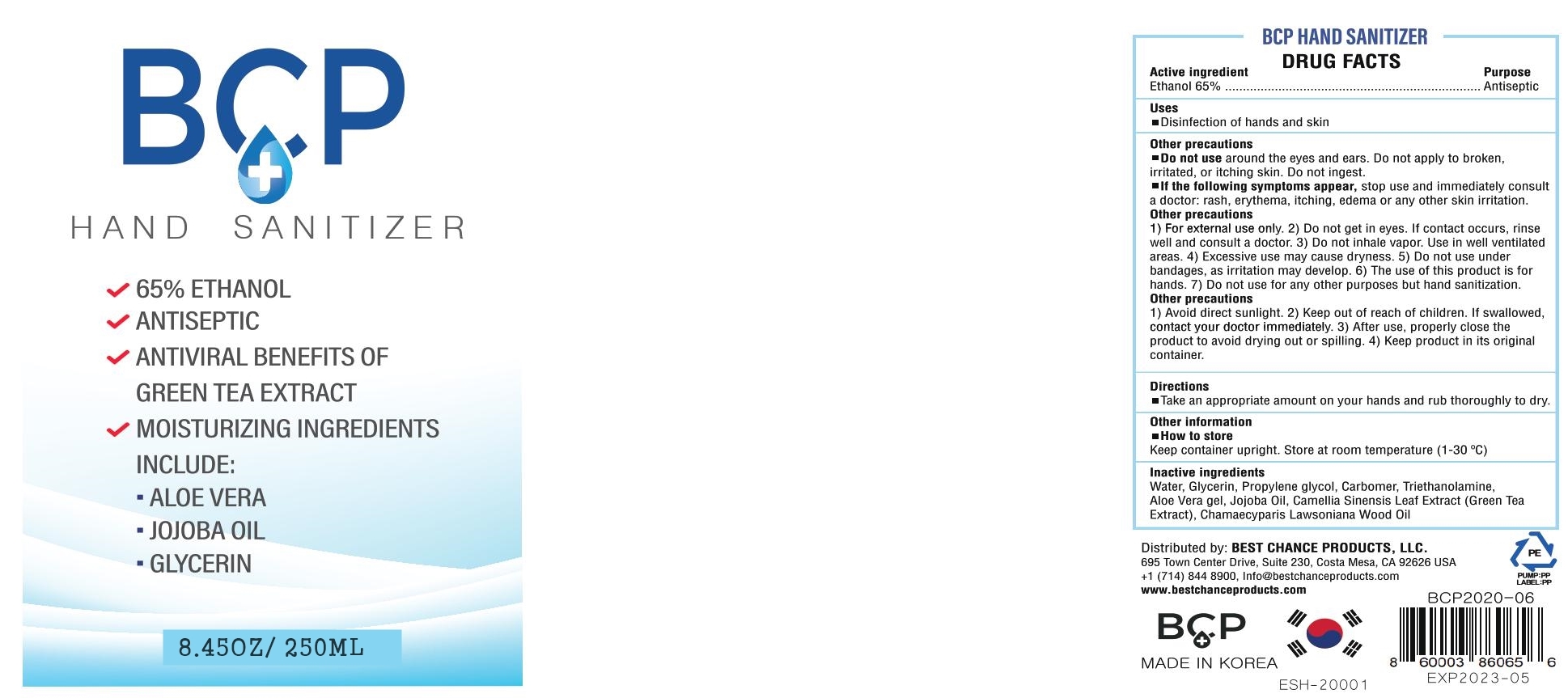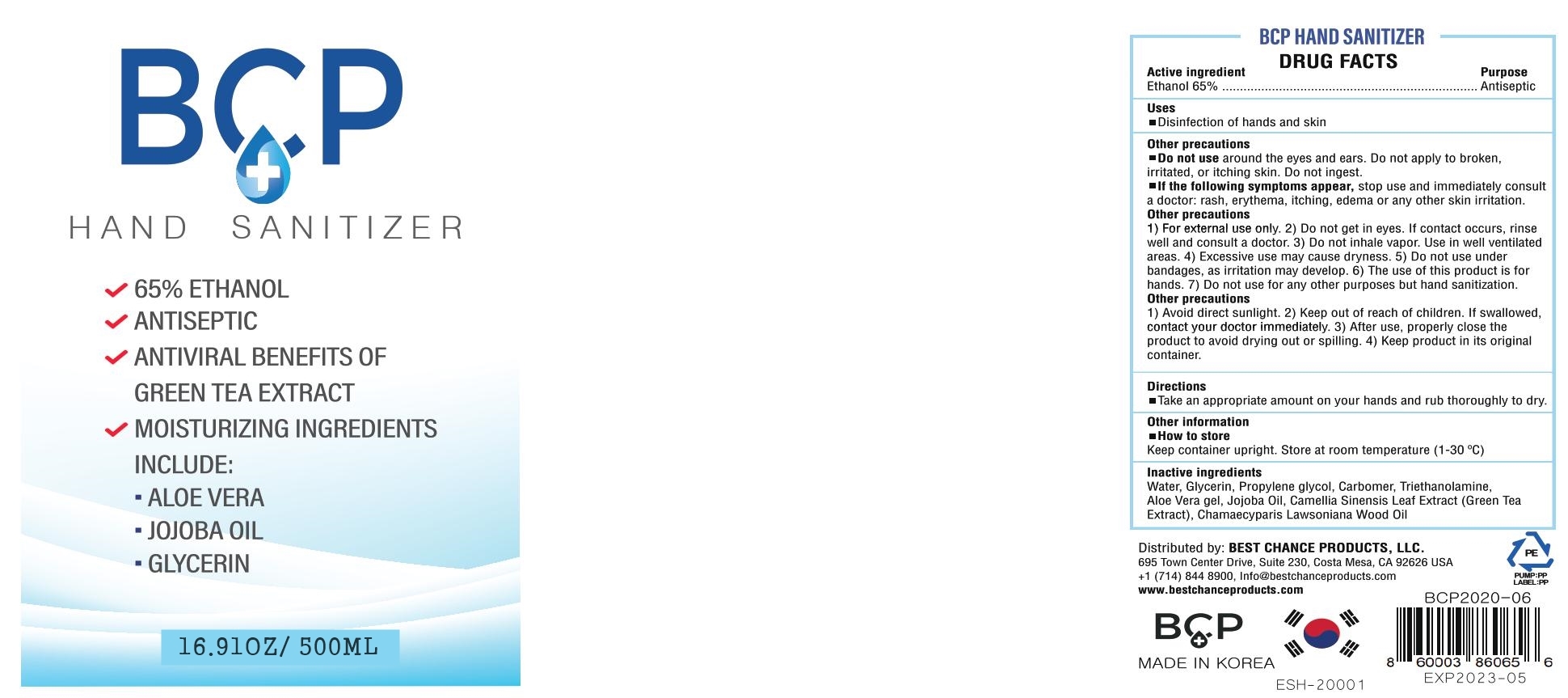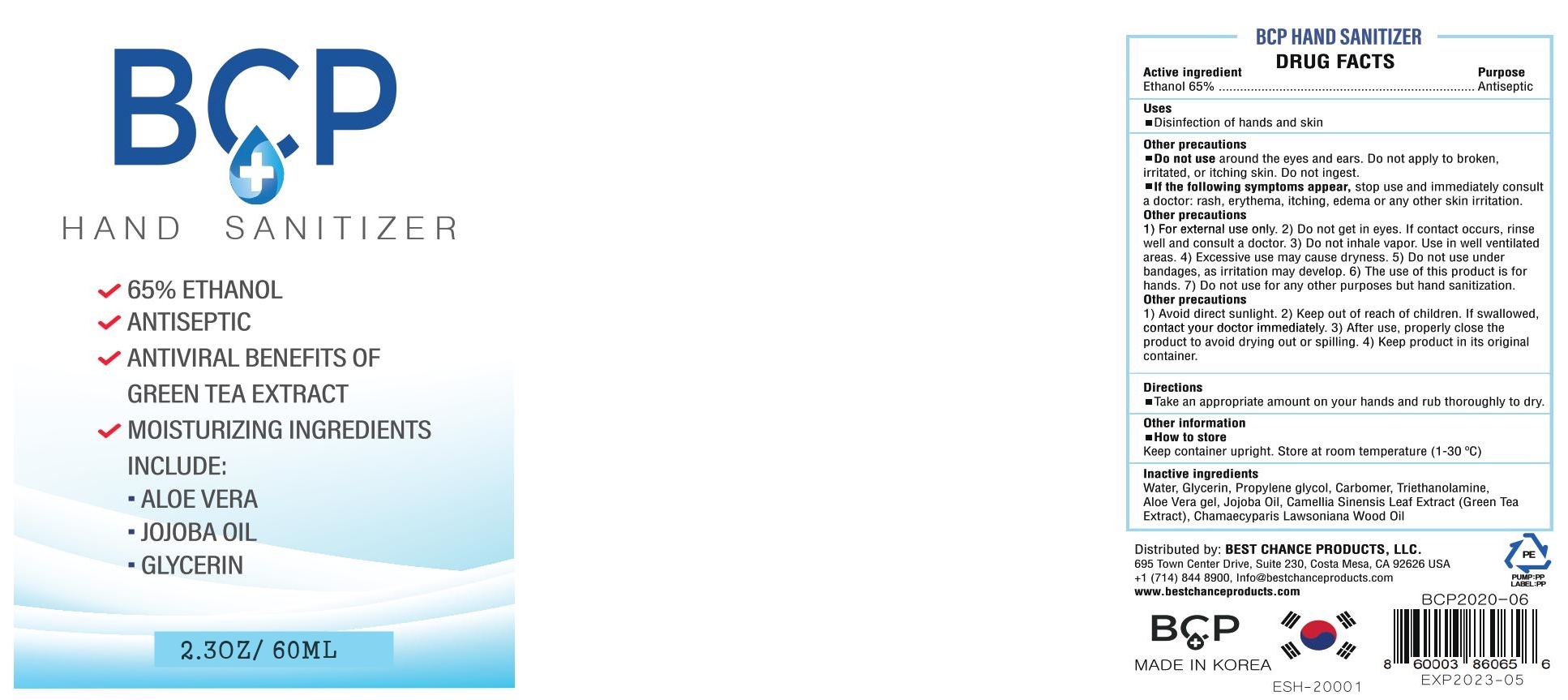 DRUG LABEL: BCP HAND SANITIZER
NDC: 78252-301 | Form: GEL
Manufacturer: Best Chance Products, LLC
Category: otc | Type: HUMAN OTC DRUG LABEL
Date: 20200612

ACTIVE INGREDIENTS: ALCOHOL 65 mL/100 mL
INACTIVE INGREDIENTS: WATER 34.13 mL/100 mL; PROPYLENE GLYCOL 0.2 mL/100 mL; CARBOMER 940 0.2 mL/100 mL; ALOE VERA LEAF 0.02 mL/100 mL; JOJOBA OIL 0.02 mL/100 mL; GREEN TEA LEAF 0.02 mL/100 mL; CHAMAECYPARIS LAWSONIANA WOOD OIL 0.01 mL/100 mL; GLYCERIN 0.2 mL/100 mL; TROLAMINE 0.2 mL/100 mL

sanitizer

ACTIVE INGREDIENTS

ethanol alchol 65%

PURPOSE

Antiseptic

INACTIVE INGREDIENT

Water, Glycerin, Propylene glycol, Cabomer940, Aloe Vera gel, Triethanolamine, Jojoba Oil
green tea Leaf Extract, Chamaecyparis Lawsoniana Wood Oil

USE

Sanitizer to help reduce bacteria that potentially can cause disease. For use when soap and water are not available.

OTHER INFORMATION

1. Store in cool and shady place, between 15-30C (59-86F)

2. May discolor certain fabrics or surfaces.

Stop use and ask a doctor if sings symptoms as follows

1) signs of irritation and/or rash appears

(2) signs of abnormality as above after exposed to sunlight.

KEEP OUT OF REACH OF CHILDREN.

If swallowed, get medical help or contact a Poison Control Center right away.

Do not use

In children less than 2 months of age.
On open skin wounds

WARNING

Flammable. Keep away from heat or flame. Use only as intended and according to the directions of use.

When using this product

keep out of eyes, ears, and mouth. In case of contact with eyes, rinse eyes thorough with water.

Directions

Watch for children under 6 years of age to avoid rubbing, rubbing them on their backs, or drinking this product.

PAKAGE LABEL

60ml 78252-301-01

125ml 78252-301-02

250ml 78252-301-03

500ml 78252-301-04

1000ml 78252-301-05

200L 78252-301-06

1000L 78252-301-07